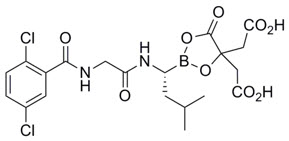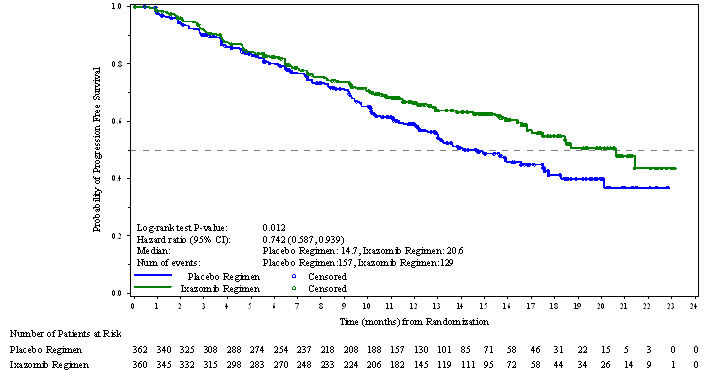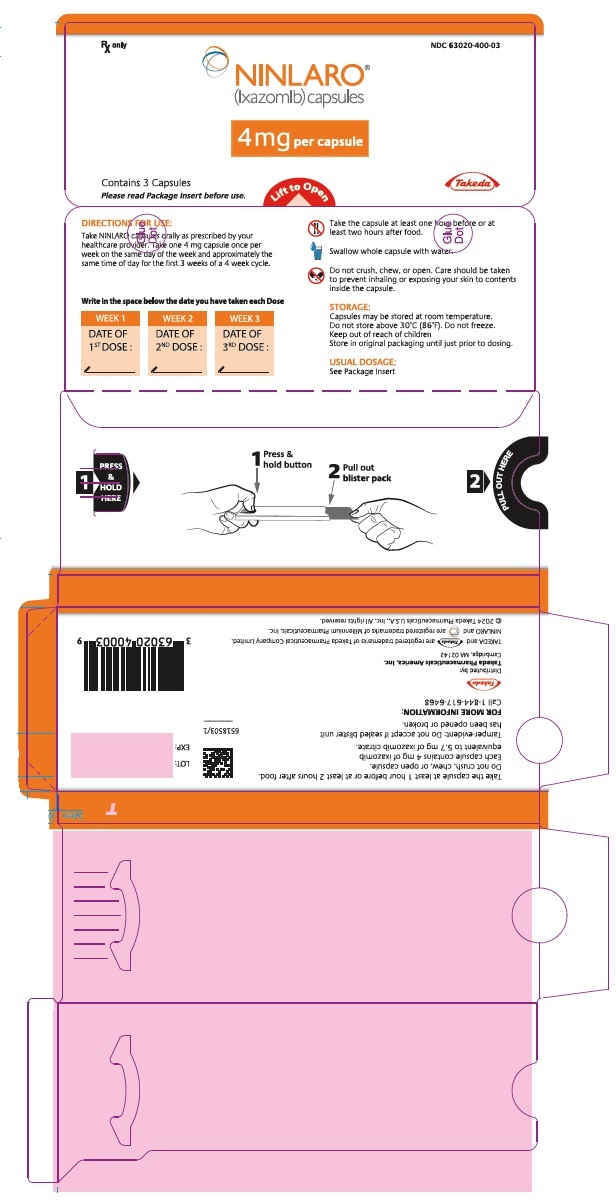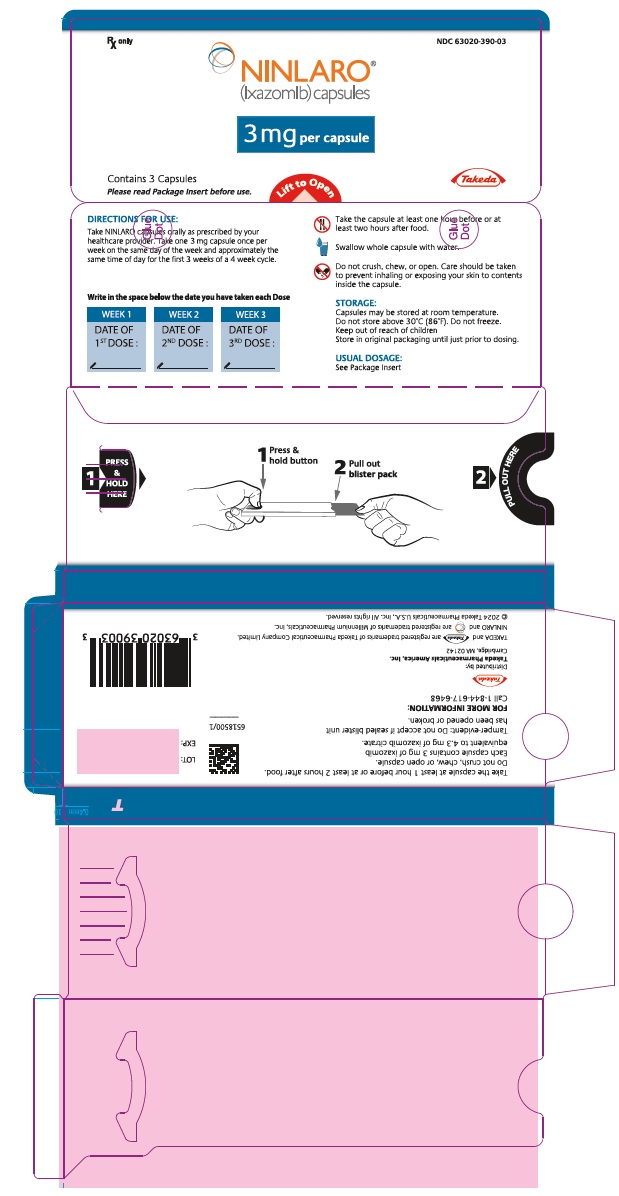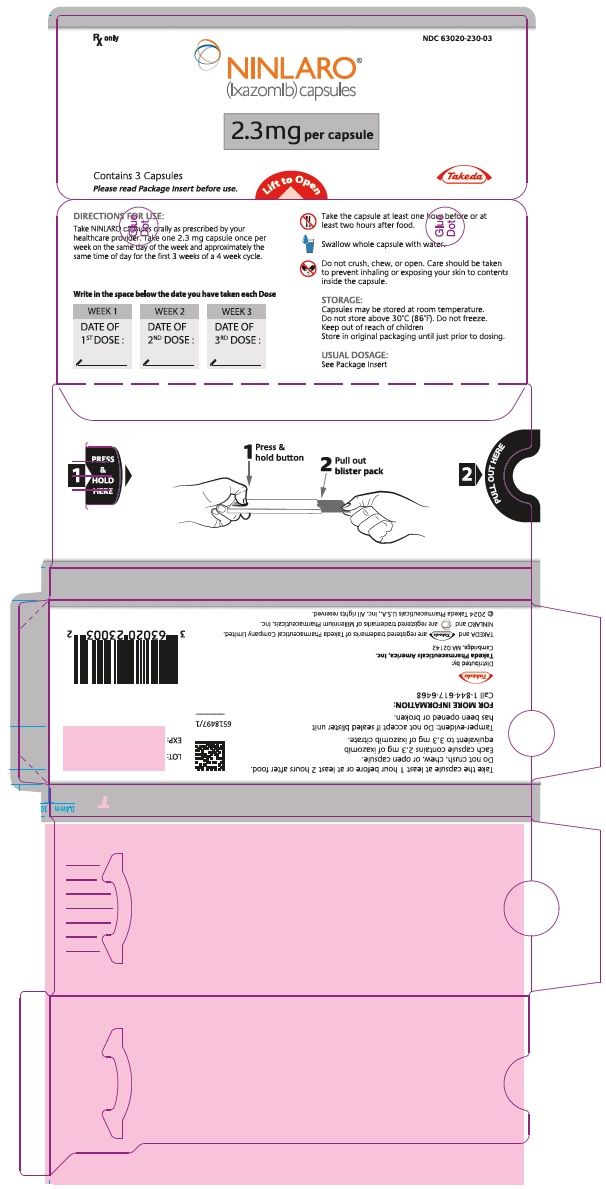 DRUG LABEL: NINLARO
NDC: 63020-400 | Form: CAPSULE
Manufacturer: Takeda Pharmaceuticals America, Inc.
Category: prescription | Type: HUMAN PRESCRIPTION DRUG LABEL
Date: 20250818

ACTIVE INGREDIENTS: ixazomib citrate 4 mg/1 1
INACTIVE INGREDIENTS: microcrystalline cellulose; talc; magnesium stearate

HIGHLIGHTS OF PRESCRIBING INFORMATION

These highlights do not include all the information needed to use NINLARO safely and effectively. See full prescribing information for NINLARO.
NINLARO® (ixazomib) capsules, for oral use
Initial U.S. Approval: 2015

RECENT MAJOR CHANGES

Warnings and Precautions, Cutaneous Reactions (5.5) | 3/2024

1 INDICATIONS AND USAGE

NINLARO is a proteasome inhibitor indicated in combination with lenalidomide and dexamethasone for the treatment of patients with multiple myeloma who have received at least one prior therapy. (1)

Limitations of Use: NINLARO is not recommended for use in the maintenance setting or in newly diagnosed multiple myeloma in combination with lenalidomide and dexamethasone outside of controlled clinical trials. (1)

2 DOSAGE AND ADMINISTRATION

- Recommended starting dose of 4 mg taken orally on Days 1, 8, and 15 of a 28-day cycle. (2.1)
- Dose should be taken at least one hour before or at least two hours after food. (2.1)

3 DOSAGE FORMS AND STRENGTHS

Capsules: 4 mg, 3 mg, and 2.3 mg (3)

4 CONTRAINDICATIONS

None. (4)

5 WARNINGS AND PRECAUTIONS

- Thrombocytopenia: Monitor platelet counts at least monthly during treatment and adjust dosing, as needed. (2.2, 5.1)
- Gastrointestinal Toxicities: Adjust dosing for severe diarrhea, constipation, nausea, and vomiting, as needed. (2.2, 5.2)
- Peripheral Neuropathy: Monitor patients for symptoms of peripheral neuropathy and adjust dosing, as needed. (2.2, 5.3)
- Peripheral Edema: Monitor for fluid retention. Investigate for underlying causes, when appropriate. Adjust dosing, as needed. (2.2, 5.4)
- Cutaneous Reactions: Monitor patients for rash and adjust dosing, as needed. (2.2, 5.5)
- Thrombotic Microangiopathy: Monitor for signs and symptoms. Discontinue NINLARO if suspected. (5.6)
- Hepatotoxicity: Monitor hepatic enzymes during treatment. (5.7)
- Embryo-Fetal Toxicity: NINLARO can cause fetal harm. Advise patients of the potential risk to a fetus and to use effective non-hormonal contraception. (5.8, 8.1, 8.3)
- Increased Mortality in Patients Treated with NINLARO in the Maintenance Setting: Treatment of patients with NINLARO for multiple myeloma in the maintenance setting is not recommended outside of controlled trials. (5.9)

6 ADVERSE REACTIONS

The most common adverse reactions (≥20%) are thrombocytopenia, neutropenia, diarrhea, constipation, peripheral neuropathy, nausea, peripheral edema, rash, vomiting, and bronchitis. (6.1)

To report SUSPECTED ADVERSE REACTIONS, contact Takeda Pharmaceuticals at 1-844-617-6468 or FDA at 1-800-FDA-1088 or www.fda.gov/medwatch.

7 DRUG INTERACTIONS

Strong CYP3A inducers: Avoid concomitant use with NINLARO. (7.1, 12.3)

8 USE IN SPECIFIC POPULATIONS

- Hepatic Impairment: Reduce the NINLARO starting dose to 3 mg in patients with moderate or severe hepatic impairment. (2.3, 8.6)
- Renal Impairment: Reduce the NINLARO starting dose to 3 mg in patients with severe renal impairment or end-stage renal disease requiring dialysis. (2.4, 8.7)
- Lactation: Advise not to breastfeed. (8.2)

FULL PRESCRIBING INFORMATION

1 INDICATIONS AND USAGE

NINLARO is indicated in combination with lenalidomide and dexamethasone for the treatment of patients with multiple myeloma who have received at least one prior therapy.

Limitations of Use: NINLARO is not recommended for use in the maintenance setting or in newly diagnosed multiple myeloma in combination with lenalidomide and dexamethasone outside of controlled clinical trials [see Warnings and Precautions (5.9) and Clinical Studies (14.2, 14.3)].

2 DOSAGE AND ADMINISTRATION

2.1 Dosing and Administration Guidelines

NINLARO in combination with lenalidomide and dexamethasone

The recommended starting dose of NINLARO is 4 mg administered orally once a week on Days 1, 8, and 15 of a 28-day treatment cycle.

The recommended starting dose of lenalidomide is 25 mg administered daily on Days 1 through 21 of a 28-day treatment cycle.

The recommended starting dose of dexamethasone is 40 mg administered on Days 1, 8, 15, and 22 of a 28-day treatment cycle.

Table 1: Dosing Schedule for NINLARO taken with Lenalidomide and Dexamethasone ✔ Take medicine
28-Day Cycle (a 4-week cycle)
 | Week 1 |  | Week 2 |  | Week 3 |  | Week 4
 | Day 1 | Days 2-7 | Day 8 | Days 9-14 | Day 15 | Days 16-21 | Day 22 | Days 23-28
NINLARO | ✔ |  | ✔ |  | ✔
Lenalidomide | ✔ | ✔ Daily | ✔ | ✔ Daily | ✔ | ✔ Daily
Dexamethasone | ✔ |  | ✔ |  | ✔ |  | ✔

For additional information regarding lenalidomide and dexamethasone, refer to their prescribing information.

NINLARO should be taken once a week on the same day and at approximately the same time for the first three weeks of a four week cycle. The importance of carefully following all dosage instructions should be discussed with patients starting treatment. Instruct patients to take the recommended dosage as directed, because overdosage has led to deaths [see Overdosage (10)].

NINLARO should be taken at least one hour before or at least two hours after food [see Clinical Pharmacology (12.3)]. The whole capsule should be swallowed with water. The capsule should not be crushed, chewed or opened [see How Supplied/Storage and Handling (16)].

If a NINLARO dose is delayed or missed, the dose should be taken only if the next scheduled dose is ≥72 hours away. A missed dose should not be taken within 72 hours of the next scheduled dose. A double dose should not be taken to make up for the missed dose.

If vomiting occurs after taking a dose, the patient should not repeat the dose. The patient should resume dosing at the time of the next scheduled dose.

Prior to initiating a new cycle of therapy:

- Absolute neutrophil count should be at least 1,000/mm^3
- Platelet count should be at least 75,000/mm^3
- Non-hematologic toxicities should, at the healthcare provider's discretion, generally be recovered to patient's baseline condition or Grade 1 or lower

Treatment should be continued until disease progression or unacceptable toxicity.

Concomitant Medications

Consider antiviral prophylaxis in patients being treated with NINLARO to decrease the risk of herpes zoster reactivation [see Adverse Reactions (6.1)].

2.2 Dosage Modification Guidelines

The NINLARO dose reduction steps are presented in Table 2 and the dosage modification guidelines are provided in Table 3.

Table 2: NINLARO Dose Reductions due to Adverse Reactions
Recommended starting dose [Recommended starting dose of 3 mg in patients with moderate or severe hepatic impairment, severe renal impairment or end-stage renal disease requiring dialysis [see Dosage and Administration (2.3, 2.4)].] | First reduction to | Second reduction to | Discontinue
4 mg | 3 mg | 2.3 mg | Discontinue

An alternating dose modification approach is recommended for NINLARO and lenalidomide for thrombocytopenia, neutropenia, and rash as described in Table 3. Refer to the lenalidomide prescribing information if dose reduction is needed for lenalidomide.

Table 3: Dosage Modifications Guidelines for NINLARO in Combination with Lenalidomide and Dexamethasone
Hematological Toxicities | Recommended Actions
Thrombocytopenia (Platelet Count)
Platelet count less than 30,000/mm^3 | - Withhold NINLARO and lenalidomide until platelet count is at least 30,000/mm^3. - Following recovery, resume lenalidomide at the next lower dose according to its prescribing information and resume NINLARO at its most recent dose. - If platelet count falls to less than 30,000/mm^3 again, withhold NINLARO and lenalidomide until platelet count is at least 30,000/mm^3. - Following recovery, resume NINLARO at the next lower dose and resume lenalidomide at its most recent dose. [For additional occurrences, alternate dose modification of lenalidomide and NINLARO]
Neutropenia (Absolute Neutrophil Count)
Absolute neutrophil count less than 500/mm^3 | - Withhold NINLARO and lenalidomide until absolute neutrophil count is at least 500/mm^3. Consider adding G-CSF as per clinical guidelines. - Following recovery, resume lenalidomide at the next lower dose according to its prescribing information and resume NINLARO at its most recent dose. - If absolute neutrophil count falls to less than 500/mm^3 again, withhold NINLARO and lenalidomide until absolute neutrophil count is at least 500/mm^3. - Following recovery, resume NINLARO at the next lower dose and resume lenalidomide at its most recent dose.
Non-Hematological Toxicities | Recommended Actions
Rash
Grade [Grading based on National Cancer Institute Common Terminology Criteria (CTCAE) Version 4.03] 2 or 3 | - Withhold lenalidomide until rash recovers to Grade 1 or lower. - Following recovery, resume lenalidomide at the next lower dose according to its prescribing information. - If Grade 2 or 3 rash occurs again, withhold NINLARO and lenalidomide until rash recovers to Grade 1 or lower. - Following recovery, resume NINLARO at the next lower dose and resume lenalidomide at its most recent dose.
Grade 4 | Discontinue treatment regimen.
Peripheral Neuropathy
Grade 1 Peripheral Neuropathy with Pain or Grade 2 Peripheral Neuropathy | - Withhold NINLARO until peripheral neuropathy recovers to Grade 1 or lower without pain or patient's baseline. - Following recovery, resume NINLARO at its most recent dose.
Grade 2 Peripheral Neuropathy with Pain or Grade 3 Peripheral Neuropathy | - Withhold NINLARO. Toxicities should, at the healthcare provider's discretion, generally recover to patient's baseline condition or Grade 1 or lower prior to resuming NINLARO. - Following recovery, resume NINLARO at the next lower dose.
Grade 4 Peripheral Neuropathy | Discontinue treatment regimen.
Other Non-Hematological Toxicities
Other Grade 3 or 4 Non-Hematological Toxicities | - Withhold NINLARO. Toxicities should, at the healthcare provider's discretion, generally recover to patient's baseline condition or Grade 1 or lower prior to resuming NINLARO. - If attributable to NINLARO, resume NINLARO at the next lower dose following recovery.

2.3 Dosage in Patients with Hepatic Impairment

Reduce the starting dose of NINLARO to 3 mg in patients with moderate (total bilirubin greater than 1.5-3 × ULN) or severe (total bilirubin greater than 3 × ULN) hepatic impairment [see Use in Specific Populations (8.6) and Clinical Pharmacology (12.3)].

2.4 Dosage in Patients with Renal Impairment

Reduce the starting dose of NINLARO to 3 mg in patients with severe renal impairment (creatinine clearance less than 30 mL/min) or end-stage renal disease (ESRD) requiring dialysis. NINLARO is not dialyzable and therefore can be administered without regard to the timing of dialysis [see Use in Specific Populations (8.7) and Clinical Pharmacology (12.3)].

Refer to the lenalidomide prescribing information for dosing recommendations in patients with renal impairment.

3 DOSAGE FORMS AND STRENGTHS

NINLARO is available in the following capsules:

- 4 mg ixazomib: Light orange gelatin capsule imprinted with "Takeda" on the cap and "4 mg" on the body in black ink.
- 3 mg ixazomib: Light grey gelatin capsule imprinted with "Takeda" on the cap and "3 mg" on the body in black ink.
- 2.3 mg ixazomib: Light pink gelatin capsule imprinted with "Takeda" on the cap and "2.3 mg" on the body in black ink.

4 CONTRAINDICATIONS

None.

5 WARNINGS AND PRECAUTIONS

5.1 Thrombocytopenia

Thrombocytopenia has been reported with NINLARO with platelet nadirs typically occurring between Days 14-21 of each 28-day cycle and recovery to baseline by the start of the next cycle [see Adverse Reactions (6.1)]. Grade 3 thrombocytopenia was reported in 17% of patients in the NINLARO regimen and Grade 4 thrombocytopenia was reported in 13% in the NINLARO regimen. The rate of platelet transfusions was 10% in the NINLARO regimen and 7% in the placebo regimen.

Monitor platelet counts at least monthly during treatment with NINLARO. Consider more frequent monitoring during the first three cycles. Manage thrombocytopenia with dose modifications [see Dosage and Administration (2.2)] and platelet transfusions as per standard medical guidelines.

5.2 Gastrointestinal Toxicities

Diarrhea, constipation, nausea, and vomiting have been reported with NINLARO, occasionally requiring use of antidiarrheal and antiemetic medications, and supportive care. Diarrhea was reported in 52% of patients in the NINLARO regimen and 43% in the placebo regimen, constipation in 35% and 28%, respectively, nausea in 32% and 23%, respectively, and vomiting in 26% and 13%, respectively. Diarrhea resulted in discontinuation of one or more of the three drugs in 3% of patients in the NINLARO regimen and 2% of patients in the placebo regimen [see Adverse Reactions (6.1)]. Adjust dosing for Grade 3 or 4 symptoms [see Dosage and Administration (2.2)].

5.3 Peripheral Neuropathy

The majority of peripheral neuropathy adverse reactions were Grade 1 (18% in the NINLARO regimen and 16% in the placebo regimen) and Grade 2 (11% in the NINLARO regimen and 6% in the placebo regimen) [see Adverse Reactions (6.1)]. Grade 3 adverse reactions of peripheral neuropathy were reported at 2% in both regimens.

The most commonly reported reaction was peripheral sensory neuropathy (24% and 17% in the NINLARO and placebo regimen, respectively). Peripheral motor neuropathy was not commonly reported in either regimen (<1%). Peripheral neuropathy resulted in discontinuation of one or more of the three drugs in 4% of patients in the NINLARO regimen and <1% of patients in the placebo regimen. Patients should be monitored for symptoms of neuropathy. Patients experiencing new or worsening peripheral neuropathy may require dose modification [see Dosage and Administration (2.2)].

5.4 Peripheral Edema

Peripheral edema was reported in 27% and 21% of patients in the NINLARO and placebo regimens, respectively. The majority of peripheral edema adverse reactions were Grade 1 (17% in the NINLARO regimen and 14% in the placebo regimen) and Grade 2 (7% in the NINLARO regimen and 6% in the placebo regimen).

Grade 3 peripheral edema was reported in 2% and 1% of patients in the NINLARO and placebo regimens, respectively [see Adverse Reactions (6.1)]. Peripheral edema resulted in discontinuation of one or more of the three drugs in <1% of patients in both regimens. Evaluate for underlying causes and provide supportive care, as necessary. Adjust dosing of dexamethasone per its prescribing information or NINLARO for Grade 3 or 4 symptoms [see Dosage and Administration (2.2)].

5.5 Cutaneous Reactions

Rash was reported in 27% of patients in the NINLARO regimen and 16% of patients in the placebo regimen. The majority of the rash adverse reactions were Grade 1 (15% in the NINLARO regimen and 9% in the placebo regimen) or Grade 2 (9% in the NINLARO regimen and 4% in the placebo regimen) [see Adverse Reactions (6.1)]. Grade 3 rash was reported in 3% of patients in the NINLARO regimen and 2% of patients in the placebo regimen. Serious adverse reactions of rash were reported in <1% of patients in the NINLARO regimen. The most common type of rash reported in both regimens included maculo-papular and macular rash. Rash resulted in discontinuation of one or more of the three drugs in <1% of patients in both regimens. Manage rash with supportive care or with dose modification if Grade 2 or higher [see Dosage and Administration (2.2)].

Stevens-Johnson syndrome and toxic epidermal necrolysis, including fatal cases, have been reported with NINLARO [see Adverse Reactions (6.1, 6.2)]. If Stevens-Johnson syndrome or toxic epidermal necrolysis occurs, discontinue NINLARO and manage as clinically indicated.

5.6 Thrombotic Microangiopathy

Cases, sometimes fatal, of thrombotic microangiopathy, including thrombotic thrombocytopenic purpura/hemolytic uremic syndrome (TTP/HUS), have been reported in patients who received NINLARO [see Adverse Reactions (6.1)]. Monitor for signs and symptoms of TTP/HUS. If the diagnosis is suspected, stop NINLARO and evaluate. If the diagnosis of TTP/HUS is excluded, consider restarting NINLARO. The safety of reinitiating NINLARO therapy in patients previously experiencing TTP/HUS is not known.

5.7 Hepatotoxicity

Drug-induced liver injury, hepatocellular injury, hepatic steatosis, hepatitis cholestatic and hepatotoxicity have each been reported in <1% of patients treated with NINLARO [see Adverse Reactions (6.1)]. Hepatotoxicity has been reported (10% in the NINLARO regimen and 9% in the placebo regimen). Monitor hepatic enzymes regularly and adjust dosing for Grade 3 or 4 symptoms [see Dosage and Administration (2.2)].

5.8 Embryo-Fetal Toxicity

NINLARO can cause fetal harm when administered to a pregnant woman based on the mechanism of action and findings in animal studies. Ixazomib caused embryo-fetal toxicity in pregnant rats and rabbits at doses resulting in exposures that were slightly higher than those observed in patients receiving the recommended dose. Advise pregnant women of the potential risk to a fetus. Advise females of reproductive potential to use effective non-hormonal contraception during treatment with NINLARO and for 90 days following the last dose. Advise males with female partners of reproductive potential to use effective contraception during treatment with NINLARO and for 90 days following the last dose [see Drug Interactions (7.1) and Use in Specific Populations (8.1, 8.3)].

5.9 Increased Mortality in Patients Treated with NINLARO in the Maintenance Setting

In two prospective randomized clinical trials in multiple myeloma in the maintenance setting, treatment with NINLARO resulted in increased deaths. Treatment of patients with NINLARO for multiple myeloma in the maintenance setting is not recommended outside of controlled trials [see Clinical Studies (14.2)].

6 ADVERSE REACTIONS

The following adverse reactions are described in detail in other sections of the prescribing information:

- Thrombocytopenia [see Warnings and Precautions (5.1)]
- Gastrointestinal Toxicities [see Warnings and Precautions (5.2)]
- Peripheral Neuropathy [see Warnings and Precautions (5.3)]
- Peripheral Edema [see Warnings and Precautions (5.4)]
- Cutaneous Reactions [see Warnings and Precautions (5.5)]
- Thrombotic Microangiopathy [see Warnings and Precautions (5.6)]
- Hepatotoxicity [see Warnings and Precautions (5.7)]

6.1 Clinical Trials Experience

Because clinical trials are conducted under widely varying conditions, adverse reaction rates observed in the clinical trials of a drug cannot be directly compared to rates in the clinical trials of another drug and may not reflect the rates observed in practice.

The safety population from the randomized, double-blind, placebo-controlled clinical study included 720 patients with relapsed and/or refractory multiple myeloma, who received NINLARO in combination with lenalidomide and dexamethasone (NINLARO regimen; N=361) or placebo in combination with lenalidomide and dexamethasone (placebo regimen; N=359).

The most frequently reported adverse reactions (≥20% with a difference of ≥5% compared to placebo) in the NINLARO regimen were thrombocytopenia, neutropenia, diarrhea, constipation, peripheral neuropathy, nausea, peripheral edema, rash, vomiting, and bronchitis. Serious adverse reactions reported in ≥2% of patients in the NINLARO regimen included diarrhea (3%), thrombocytopenia (2%) and bronchitis (2%). One or more of the three drugs was permanently discontinued in 4% of patients reporting peripheral neuropathy, 3% of patients reporting diarrhea and 2% of patients reporting thrombocytopenia. Permanent discontinuation of NINLARO due to an adverse reaction occurred in 10% of patients.

Table 4 summarizes the non-hematologic adverse reactions occurring in at least 5% of patients with at least a 5% difference between the NINLARO regimen and the placebo regimen.

Table 4: Non-Hematologic Adverse Reactions Occurring in ≥5% of Patients with a ≥5% Difference Between the NINLARO Regimen and the Placebo Regimen (All Grades, Grade 3 and Grade 4)
System Organ Class / Preferred Term | NINLARO + Lenalidomide and Dexamethasone N=361 |  |  | Placebo + Lenalidomide and Dexamethasone N=359
System Organ Class / Preferred Term | % |  |  | %
System Organ Class / Preferred Term | All Grades | Grade 3 | Grade 4 | All Grades | Grade 3 | Grade 4
Gastrointestinal disorders
Diarrhea | 52 | 10 | 0 | 43 | 3 | 0
Constipation | 35 | <1 | 0 | 28 | <1 | 0
Nausea | 32 | 2 | 0 | 23 | 0 | 0
Vomiting | 26 | 1 | 0 | 13 | <1 | 0
Nervous system disorders
Peripheral neuropathies [Represents a pooling of preferred terms] | 32 | 2 | 0 | 24 | 2 | 0
Musculoskeletal and connective tissue disorders
Back pain [At the time of the final analysis, these adverse reactions no longer met the criterion for a ≥5% difference between the NINLARO regimen and the placebo regimen.] | 27 | <1 | 0 | 24 | 3 | 0
Infections and infestations
Upper respiratory tract infection | 27 | 1 | 0 | 23 | 1 | 0
Bronchitis | 22 | 2 | 0 | 17 | 2 | <1
Skin and subcutaneous tissue disorders
Rash | 27 | 3 | 0 | 16 | 2 | 0
General disorders and administration site conditions
Edema peripheral | 27 | 2 | 0 | 21 | 1 | 0
Note: Adverse reactions included as preferred terms are based on MedDRA version 23.0.

Table 5 represents pooled information from adverse event and laboratory data.

Table 5: Thrombocytopenia and Neutropenia
 | NINLARO + Lenalidomide and Dexamethasone N=361 |  | Placebo + Lenalidomide and Dexamethasone N=359
 | % |  | %
 | Any Grade | Grade 3-4 | Any Grade | Grade 3-4
Thrombocytopenia | 85 | 30 | 67 | 14
Neutropenia | 74 | 34 | 70 | 37

Herpes Zoster

Herpes zoster was reported in 6% of patients in the NINLARO regimen and 3% of patients in the placebo regimen. Antiviral prophylaxis was allowed at the healthcare provider's discretion. Patients treated in the NINLARO regimen who received antiviral prophylaxis had a lower incidence (1%) of herpes zoster infection compared to patients who did not receive prophylaxis (10%).

Eye Disorders

Eye disorders were reported with many different preferred terms but in aggregate, the frequency was 38% in patients in the NINLARO regimen. The most common adverse reactions of the eyes were cataract (15%), conjunctivitis (9%), blurred vision (7%), and dry eye (6%).

Other Clinical Trials Experience

The following serious adverse reactions have each been reported at a frequency of <1% in patients treated with NINLARO: acute febrile neutrophilic dermatosis (Sweet's syndrome), Stevens-Johnson syndrome, transverse myelitis, posterior reversible encephalopathy syndrome, tumor lysis syndrome, and thrombotic thrombocytopenic purpura.

6.2 Postmarketing Experience

The following adverse reactions have been identified during post-approval use of NINLARO. Because these reactions are reported voluntarily from a population of uncertain size, it is not always possible to reliably estimate their frequency or establish a causal relationship to drug exposure.

Immune system disorders: Angioedema

Skin and subcutaneous tissue disorders: Toxic epidermal necrolysis

7 DRUG INTERACTIONS

7.1 Strong CYP3A Inducers

Avoid concomitant administration of NINLARO with strong CYP3A inducers (such as rifampin, phenytoin, carbamazepine, and St. John's Wort) [see Clinical Pharmacology (12.3)].

8 USE IN SPECIFIC POPULATIONS

8.1 Pregnancy

Risk Summary

Based on its mechanism of action [see Clinical Pharmacology (12.1)] and data from animal reproduction studies, NINLARO can cause fetal harm when administered to a pregnant woman. There are no available data on NINLARO use in pregnant women to evaluate drug-associated risk. Ixazomib caused embryo-fetal toxicity in pregnant rats and rabbits at doses resulting in exposures that were slightly higher than those observed in patients receiving the recommended dose (see Data). Advise pregnant women of the potential risk to a fetus.

In the U.S. general population, the estimated background risk of major birth defects and miscarriage in clinically recognized pregnancies is 2-4% and 15-20%, respectively.

Data

Animal Data

In an embryo-fetal development study in pregnant rabbits there were increases in fetal skeletal variations/abnormalities (fused caudal vertebrae, number of lumbar vertebrae, and full supernumerary ribs) at doses that were also maternally toxic (≥0.3 mg/kg). Exposures in the rabbit at 0.3 mg/kg were 1.9 times the clinical time averaged exposures at the recommended dose of 4 mg. In a rat dose range-finding embryo-fetal development study, at doses that were maternally toxic, there were decreases in fetal weights, a trend towards decreased fetal viability, and increased post-implantation losses at 0.6 mg/kg. Exposures in rats at the dose of 0.6 mg/kg was 2.5 times the clinical time averaged exposures at the recommended dose of 4 mg.

8.2 Lactation

Risk Summary

There are no data on the presence of ixazomib or its metabolites in human milk, the effects of the drug on the breast fed infant, or the effects of the drug on milk production. Because of the potential for serious adverse reactions from NINLARO in a breastfed infant, advise women not to breastfeed during treatment with NINLARO and for 90 days after the last dose.

8.3 Females and Males of Reproductive Potential

NINLARO can cause fetal harm when administered to pregnant women [see Use in Specific Populations (8.1)].

Pregnancy Testing

Verify pregnancy status in females of reproductive potential prior to initiating NINLARO.

Contraception

Females

Advise females of reproductive potential to use effective non-hormonal contraception during treatment with NINLARO and for 90 days after the last dose. Dexamethasone is known to be a weak to moderate inducer of CYP3A4 as well as other enzymes and transporters. Because NINLARO is administered with dexamethasone, the risk for reduced efficacy of contraceptives needs to be considered [see Drug Interactions (7.1)].

Males

Advise males with female partners of reproductive potential to use effective contraception during treatment with NINLARO and for 90 days after the last dose.

8.4 Pediatric Use

Safety and effectiveness of NINLARO have not been established in pediatric patients.

8.5 Geriatric Use

Of the total number of subjects in clinical studies of NINLARO, 55% were 65 and over, while 17% were 75 and over. No overall differences in safety or effectiveness were observed between these subjects and younger subjects, and other reported clinical experience has not identified differences in responses between the elderly and younger patients, but greater sensitivity of some older individuals cannot be ruled out.

8.6 Hepatic Impairment

In patients with moderate or severe hepatic impairment, the mean AUC increased by 20% when compared to patients with normal hepatic function. Reduce the starting dose of NINLARO in patients with moderate or severe hepatic impairment [see Dosage and Administration (2.3), Clinical Pharmacology (12.3)].

8.7 Renal Impairment

In patients with severe renal impairment or ESRD requiring dialysis, the mean AUC increased by 39% when compared to patients with normal renal function. Reduce the starting dose of NINLARO in patients with severe renal impairment or ESRD requiring dialysis. NINLARO is not dialyzable and therefore can be administered without regard to the timing of dialysis [see Dosage and Administration (2.4), Clinical Pharmacology (12.3)].

10 OVERDOSAGE

Overdosage, including fatal overdosage, has been reported in patients taking NINLARO. Manifestations of overdosage include adverse reactions reported at the recommended dosage [see Dosage and Administration (2.1), Adverse Reactions (6.1)]. Serious adverse reactions reported with overdosage include severe nausea, vomiting, diarrhea, aspiration pneumonia, multiple organ failure and death.

In the event of an overdosage, monitor for adverse reactions and provide appropriate supportive care. NINLARO is not dialyzable.

11 DESCRIPTION

Ixazomib is a proteasome inhibitor. Ixazomib citrate, a prodrug, rapidly hydrolyzes under physiological conditions to its biologically active form, ixazomib. The chemical name of ixazomib citrate is 1,3,2-dioxaborolane-4,4-diacetic acid, 2-[(1R)-1-[[2-[(2,5-dichlorobenzoyl)amino]acetyl]amino]-3-methylbutyl]-5-oxo- and the structural formula is:

The molecular formula for ixazomib citrate is C20H23BCl2N2O9 and its molecular weight is 517.12. Ixazomib citrate has one chiral center and is the R-stereoisomer. The solubility of ixazomib citrate in 0.1N HCl (pH 1.2) at 37°C is 0.61 mg/mL (reported as ixazomib). The solubility increases as the pH increases.

NINLARO (ixazomib) capsules for oral use contain 4, 3 or 2.3 mg of ixazomib equivalent to 5.7, 4.3 or 3.3 mg of ixazomib citrate, respectively. Inactive ingredients include microcrystalline cellulose, magnesium stearate, and talc. Capsule shells contain gelatin and titanium dioxide. The 4 mg capsule shell contains red and yellow iron oxide, the 3 mg capsule shell contains black iron oxide and the 2.3 mg capsule shell contains red iron oxide. The printing ink contains shellac, propylene glycol, potassium hydroxide, and black iron oxide.

12 CLINICAL PHARMACOLOGY

12.1 Mechanism of Action

Ixazomib is a reversible proteasome inhibitor. Ixazomib preferentially binds and inhibits the chymotrypsin-like activity of the beta 5 subunit of the 20S proteasome.

Ixazomib induced apoptosis of multiple myeloma cell lines in vitro. Ixazomib demonstrated in vitro cytotoxicity against myeloma cells from patients who had relapsed after multiple prior therapies, including bortezomib, lenalidomide, and dexamethasone. The combination of ixazomib and lenalidomide demonstrated synergistic cytotoxic effects in multiple myeloma cell lines. In vivo, ixazomib demonstrated antitumor activity in a mouse multiple myeloma tumor xenograft model.

12.2 Pharmacodynamics

Cardiac Electrophysiology

NINLARO did not prolong the QTc interval at clinically relevant exposures based on pharmacokinetic-pharmacodynamic analysis of data from 245 patients.

12.3 Pharmacokinetics

Absorption

After oral administration, the median time to achieve peak ixazomib plasma concentrations was one hour. The mean absolute oral bioavailability was 58%, based on population PK analysis. Ixazomib AUC increases in a dose proportional manner over a dose range of 0.2 to 10.6 mg.

A food effect study conducted in patients with a single 4 mg dose of ixazomib showed that a high-fat meal decreased ixazomib AUC by 28% and Cmax by 69% [see Dosage and Administration (2.1)].

Distribution

Ixazomib is 99% bound to plasma proteins and distributes into red blood cells with a blood-to-plasma ratio of 10. The steady-state volume of distribution is 543 L.

Elimination

Based on a population PK analysis, systemic clearance was approximately 1.9 L/hr with inter-individual variability of 44%. The terminal half-life (t1/2) of ixazomib was 9.5 days. Following weekly oral dosing, the accumulation ratio was determined to be 2-fold.

Metabolism

After oral administration of a radiolabeled dose, ixazomib represented 70% of total drug-related material in plasma. Metabolism by multiple CYP enzymes and non-CYP proteins is expected to be the major clearance mechanism for ixazomib. At clinically relevant ixazomib concentrations, in vitro studies using human cDNA-expressed cytochrome P450 isozymes showed that no specific CYP isozyme predominantly contributes to ixazomib metabolism. At higher than clinical concentrations, ixazomib was metabolized by multiple CYP isoforms with estimated relative contributions of 3A4 (42%), 1A2 (26%), 2B6 (16%), 2C8 (6%), 2D6 (5%), 2C19 (5%) and 2C9 (<1%).

Excretion

After administration of a single oral dose of ^14C-ixazomib to 5 patients with advanced cancer, 62% of the administered radioactivity was excreted in urine and 22% in the feces. Unchanged ixazomib accounted for <3.5% of the administered dose recovered in urine.

Specific Populations

There was no clinically meaningful effect of age (range 23-91 years), sex, body surface area (range 1.2-2.7 m^2), or race on the clearance of ixazomib based on population PK analysis.

Patients with Hepatic Impairment

The PK of ixazomib was similar in patients with normal hepatic function and in patients with mild hepatic impairment (total bilirubin ≤ ULN and AST >ULN or total bilirubin >1-1.5 × ULN and any AST) based on population PK analysis.

The PK of ixazomib was characterized in patients with normal hepatic function at 4 mg (N=12), moderate hepatic impairment at 2.3 mg (total bilirubin >1.5-3 × ULN, N=13) or severe hepatic impairment at 1.5 mg (total bilirubin >3 × ULN, N=18). Dose-normalized mean AUC was 20% higher in patients with moderate or severe hepatic impairment as compared to patients with normal hepatic function [see Dosage and Administration (2.3)].

Patients with Renal Impairment

The PK of ixazomib was similar in patients with normal renal function and in patients with mild or moderate renal impairment (creatinine clearance ≥30 mL/min) based on population PK analysis.

The PK of ixazomib was characterized at a dose of 3 mg in patients with normal renal function (creatinine clearance ≥90 mL/min, N=18), severe renal impairment (creatinine clearance <30 mL/min, N=14), or ESRD requiring dialysis (N=6). Mean AUC was 39% higher in patients with severe renal impairment or ESRD requiring dialysis as compared to patients with normal renal function. Pre- and post-dialyzer concentrations of ixazomib measured during the hemodialysis session were similar, suggesting that ixazomib is not dialyzable [see Dosage and Administration (2.4)].

Drug Interaction Studies

Effect of Other Drugs on NINLARO

Strong CYP3A Inducers

Coadministration of NINLARO with rifampin decreased ixazomib Cmax by 54% and AUC by 74% [see Drug Interactions (7.1)].

Strong CYP3A Inhibitors

Coadministration of NINLARO with clarithromycin did not result in a clinically meaningful change in the systemic exposure of ixazomib.

Strong CYP1A2 Inhibitors

Coadministration of NINLARO with strong CYP1A2 inhibitors did not result in a clinically meaningful change in the systemic exposure of ixazomib based on a population PK analysis.

Effect of NINLARO on Other Drugs

Ixazomib is neither a reversible nor a time-dependent inhibitor of CYPs 1A2, 2B6, 2C8, 2C9, 2C19, 2D6, or 3A4/5. Ixazomib did not induce CYP1A2, CYP2B6, and CYP3A4/5 activity or corresponding immunoreactive protein levels. NINLARO is not expected to produce drug-drug interactions via CYP inhibition or induction.

Transporter-Based Interactions

Ixazomib is a low affinity substrate of P-gp. Ixazomib is not a substrate of BCRP, MRP2 or hepatic OATPs. Ixazomib is not an inhibitor of P-gp, BCRP, MRP2, OATP1B1, OATP1B3, OCT2, OAT1, OAT3, MATE1, or MATE2-K. NINLARO is not expected to cause transporter-mediated drug-drug interactions.

13 NONCLINICAL TOXICOLOGY

13.1 Carcinogenesis, Mutagenesis, Impairment of Fertility

Ixazomib was not mutagenic in a bacterial reverse mutation assay (Ames assay). Ixazomib was considered positive in an in vitro clastogenicity test in human peripheral blood lymphocytes. However, in vivo, ixazomib was not clastogenic in a bone marrow micronucleus assay in mice and was negative in an in vivo comet assay in mice, as assessed in the stomach and liver. No carcinogenicity studies have been performed with ixazomib.

Developmental toxicity studies in rats and rabbits did not show direct embryo-fetal toxicity below maternally toxic doses of ixazomib. Studies of fertility and early embryonic development and pre- and postnatal toxicology were not conducted with ixazomib, but evaluation of reproductive tissues was conducted in the general toxicity studies. There were no effects due to ixazomib treatment on male or female reproductive organs in studies up to 6-months duration in rats and up to 9-months duration in dogs.

14 CLINICAL STUDIES

14.1 Multiple Myeloma in Patients Who Have Received at Least One Prior Therapy

The efficacy and safety of NINLARO in combination with lenalidomide and dexamethasone was evaluated in a randomized, double-blind, placebo-controlled, multicenter study in patients with relapsed and/or refractory multiple myeloma who had received at least one prior line of therapy. Patients who were refractory to lenalidomide or proteasome inhibitors were excluded from the study.

A total of 722 patients were randomized in a 1:1 ratio to receive either the combination of NINLARO, lenalidomide and dexamethasone (N=360; NINLARO regimen) or the combination of placebo, lenalidomide and dexamethasone (N=362; placebo regimen) until disease progression or unacceptable toxicity. Randomization was stratified according to number of prior lines of therapy (1 versus 2 or 3), myeloma International Staging System (ISS) (stage I or II versus III), and previous therapy with a proteasome inhibitor (exposed or naïve). Twenty three percent (N=166) of the patients had light chain disease and 12% (N=87) of patients had free light chain-measurable only disease.

Thromboprophylaxis was recommended for all patients in both treatment groups according to the lenalidomide prescribing information. Antiemetics were used in 19% of patients in the NINLARO regimen and 12% of patients in the placebo regimen; antivirals in 64% and 60%, respectively, and antihistamines in 27% and 19%, respectively. These medications were given to patients at the healthcare provider's discretion as prophylaxis and/or management of symptoms.

Patients received NINLARO 4 mg or placebo on Days 1, 8, and 15 plus lenalidomide (25 mg) on Days 1 through 21 and dexamethasone (40 mg) on Days 1, 8, 15, and 22 of a 28-day cycle. Patients with renal impairment received a starting dose of lenalidomide according to its prescribing information. Treatment continued until disease progression or unacceptable toxicities.

Table 6 summarizes the baseline patient and disease characteristics in the study. The baseline demographics and disease characteristics were balanced and comparable between the study regimens.

Table 6: Baseline Patient and Disease Characteristics
 | NINLARO + Lenalidomide and Dexamethasone (N = 360) | Placebo + Lenalidomide and Dexamethasone (N = 362)
Patient Characteristics
Median age in years (range) | 66 (38, 91) | 66 (30, 89)
Gender (%) Male/ Female | 58/42 | 56/44
Age Group (% [<65/ ≥65 years]) | 41/59 | 43/57
Race n (%)
White | 310 (86) | 301 (83)
Black | 7 (2) | 6 (2)
Asian | 30 (8) | 34 (9)
Other or Not Specified | 13 (4) | 21 (6)
ECOG performance status, n (%)
0 or 1 | 336 (93) | 334 (92)
2 | 18 (5) | 24 (7)
Missing | 6 (2) | 4 (1)
Creatinine clearance, n (%)
<30 mL/min | 5 (1) | 5 (1)
30-59 mL/min | 74 (21) | 95 (26)
≥60 mL/min | 281 (78) | 261 (72)
Disease Characteristics
Myeloma ISS stage, n (%)
Stage I or II | 315 (87) | 320 (88)
Stage III | 45 (13) | 42 (12)
Prior line therapies n (%)
Median (range) | 1 (1, 3) | 1 (1,3)
1 | 224 (62) | 217 (60)
2 or 3 | 136 (38) | 145 (40)
Status at Baseline n (%)
Relapsed | 276 (77) | 280 (77)
Refractory [Primary refractory, defined as best response of stable disease or disease progression on all prior lines of therapy, was documented in 7% and 6% of patients in the NINLARO regimen and placebo regimens, respectively.] | 42 (12) | 40 (11)
Relapsed and Refractory | 41 (11) | 42 (12)
Type of Prior Therapy n (%)
Bortezomib containing | 248 (69) | 250 (69)
Carfilzomib containing | 1 (<1) | 4 (1)
Thalidomide containing | 157 (44) | 170 (47)
Lenalidomide containing | 44 (12) | 44 (12)
Melphalan containing | 293 (81) | 291 (80)
Stem cell transplantation | 212 (59) | 199 (55)
High risk (deletion (del) 17, t(4:14) and/or t(14:16) | 75 (21) | 62 (17)
deletion del (17) | 36 (10) | 33 (9)

The efficacy of NINLARO was evaluated by progression-free survival (PFS) according to the 2011 International Myeloma Working Group (IMWG) Consensus Uniform Response Criteria as assessed by a blinded independent review committee (IRC) based on central lab results. Response was assessed every four weeks until disease progression.

The approval of NINLARO was based upon a statistically significant improvement in PFS of the NINLARO regimen compared to the placebo regimen. PFS results are summarized in Table 7 and shown in Figure 1.

Table 7: Progression-Free Survival and Response Rate
 | NINLARO + Lenalidomide and Dexamethasone (N = 360) | Placebo + Lenalidomide and Dexamethasone (N = 362)
Progression-free Survival
PFS Events, n (%) | 129 (36) | 157 (43)
Median (months) (95% CI) | 20.6 (17.0, NE) | 14.7 (12.9, 17.6)
Hazard Ratio [Hazard ratio is based on a stratified Cox's proportional hazard regression model. A hazard ratio less than 1 indicates an advantage for the NINLARO regimen.] (95% CI) | 0.74 (0.59, 0.94)
p-value [P-value is based on the stratified log-rank test.] | 0.012
Response Rate
Overall Response Rate, n (%) | 282 (78) | 259 (72)
Complete Response | 42 (12) | 24 (7)
Very Good Partial Response | 131 (36) | 117 (32)
Partial Response | 109 (30) | 118 (33)
NE: Not evaluable.

The median time to response was 1.1 months in the NINLARO regimen and 1.9 months in the placebo regimen. The median duration of response was 20.5 months in the NINLARO regimen and 15 months in the placebo regimen for responders in the response evaluable population.

Figure 1: Kaplan-Meier Plot of Progression-Free Survival

A non-inferential PFS analysis was conducted at a median follow up of 23 months with 372 PFS events. Hazard ratio of PFS was 0.82 (95% confidence interval [0.67, 1.0]) for NINLARO regimen versus placebo regimen, and estimated median PFS was 20 months in the NINLARO regimen and 15.9 months in the placebo regimen.

At the final analysis for OS at a median duration of follow up of approximately 85 months, median OS in the ITT population was 53.6 months for patients in the NINLARO regimen and 51.6 months for patients in the placebo regimen (HR = 0.94 [95% CI: 0.78, 1.13]).

14.2 Increased Mortality in Patients Treated with NINLARO in the Maintenance Setting

In C16019 (NCT02181413), newly diagnosed multiple myeloma patients who underwent autologous stem cell transplantation, continued on maintenance therapy for 24 months. There were 27% (105/395) deaths in the NINLARO arm compared with 26% (69/261) in the placebo arm. The hazard ratio for overall survival was 1.008 (95% CI: 0.744 - 1.367).

In C16021 (NCT02312258), newly diagnosed multiple myeloma patients, not treated with a stem cell transplant who achieved a partial response or better, continued on maintenance therapy for 24 months. There were 30% (127/425) deaths in the NINLARO arm compared with 27% (76/281) in the placebo arm. The hazard ratio for overall survival was 1.136 (95% CI: 0.853 - 1.514).

NINLARO is not recommended for use in the maintenance setting for multiple myeloma outside of controlled clinical trials [see Indications and Usage (1) and Warnings and Precautions (5.9)].

14.3 Lack of Efficacy in Patients with Newly Diagnosed Multiple Myeloma

Lack of efficacy in patients with newly diagnosed multiple myeloma was determined in a prospective randomized clinical trial.

In C16014 (NCT01850524), in newly diagnosed multiple myeloma patients, the study did not meet the prespecified primary endpoint for PFS. There were 136 (39%) deaths in the NINLARO, lenalidomide, and dexamethasone arm compared to 148 (42%) in the lenalidomide and dexamethasone arm. The hazard ratio for overall survival was 0.998 (95% CI: 0.79 - 1.261).

NINLARO is not recommended for use in combination with lenalidomide and dexamethasone in newly diagnosed multiple myeloma outside of controlled clinical trials [see Indications and Usage (1)].

15 REFERENCES

1. OSHA Hazardous Drugs. OSHA. http://www.osha.gov/SLTC/hazardousdrugs/index.html

16 HOW SUPPLIED/STORAGE AND HANDLING

How Supplied

NINLARO is supplied as follows:

Strength per Capsule | Capsule Description | Outer Carton | 3 Count Blister Pack | 1 Count Blister Pack | NDC
4 mg | Light orange, size 3, imprinted with "Takeda" on the cap and "4 mg" on the body in black ink. | Three 4 mg capsules in a carton | Each blister pack has three 4 mg capsules | Each blister pack has one 4 mg capsule | Outer carton NDC 63020-400-02 3 Count Blister Pack NDC 63020-400-03 1 Count Blister pack NDC 63020-400-01
3 mg | Light grey, size 4, imprinted with "Takeda" on the cap and "3 mg" on the body in black ink. | Three 3 mg capsules in a carton | Each blister pack has three 3 mg capsules | Each blister pack has one 3 mg capsule | Outer carton NDC 63020-390-02 3 Count Blister Pack NDC 63020-390-03 1 Count Blister pack NDC 63020-390-01
2.3 mg | Light pink, size 4, imprinted with "Takeda" on the cap and "2.3 mg" on the body in black ink. | Three 2.3 mg capsules in a carton | Each blister pack has three 2.3 mg capsules | Each blister pack has one 2.3 mg capsule | Outer carton NDC 63020-230-02 3 Count Blister Pack NDC 63020-230-03 1 Count Blister pack NDC 63020-230-01

Capsules are individually packaged in a PVC-Aluminum/Aluminum blister.

Storage

Store NINLARO at room temperature. Do not store above 30°C (86°F). Do not freeze.

Store capsules in original packaging until immediately prior to use.

Handling and Disposal

NINLARO is a hazardous drug. Follow applicable special handling and disposal procedures^1.

Do not open or crush capsules. Avoid direct contact with the capsule contents. In case of capsule breakage, avoid direct contact of capsule contents with the skin or eyes. If contact occurs with the skin, wash thoroughly with soap and water. If contact occurs with the eyes, flush thoroughly with water.

Any unused medicinal product or waste material should be disposed in accordance with local requirements.

17 PATIENT COUNSELING INFORMATION

Advise the patient to read the FDA-approved patient labeling (Patient Information).

Dosing Instructions

- Instruct patients to take NINLARO exactly as prescribed.
- Advise patients to take NINLARO once a week on the same day and at approximately the same time for the first three weeks of a four week cycle. The importance of carefully following all dosage instructions should be discussed with patients starting treatment. Advise patients to take the recommended dosage as directed, because overdosage has led to deaths [see Overdosage (10)].
- Advise patients to take NINLARO at least one hour before or at least two hours after food.
- Advise patients that NINLARO and dexamethasone should not be taken at the same time, because dexamethasone should be taken with food and NINLARO should not be taken with food.
- Advise patients to swallow the capsule whole with water. The capsule should not be crushed, chewed or opened.
- Advise patients that direct contact with the capsule contents should be avoided. In case of capsule breakage, avoid direct contact of capsule contents with the skin or eyes. If contact occurs with the skin, wash thoroughly with soap and water. If contact occurs with the eyes, flush thoroughly with water.
- If a patient misses a dose, advise them to take the missed dose as long as the next scheduled dose is ≥72 hours away. Advise patients not to take a missed dose if it is within 72 hours of their next scheduled dose.
- If a patient vomits after taking a dose, advise them not to repeat the dose but resume dosing at the time of the next scheduled dose.
- Advise patients to store capsules in original packaging, and not to remove the capsule from the packaging until just prior to taking NINLARO.
  [see Dosage and Administration (2.1)]

Thrombocytopenia

Advise patients that they may experience low platelet counts (thrombocytopenia). Signs of thrombocytopenia may include bleeding and easy bruising. [see Warnings and Precautions (5.1)].

Gastrointestinal Toxicities

Advise patients they may experience diarrhea, constipation, nausea and vomiting and to contact their healthcare providers if these adverse reactions persist. [see Warnings and Precautions (5.2)].

Peripheral Neuropathy

Advise patients to contact their healthcare providers if they experience new or worsening symptoms of peripheral neuropathy such as tingling, numbness, pain, a burning feeling in the feet or hands, or weakness in the arms or legs. [see Warnings and Precautions (5.3)].

Peripheral Edema

Advise patients to contact their healthcare providers if they experience unusual swelling of their extremities or weight gain due to swelling [see Warnings and Precautions (5.4)].

Cutaneous Reactions

Advise patients to contact their healthcare providers immediately if they experience new or worsening rash [see Warnings and Precautions (5.5)].

Thrombotic Microangiopathy

Advise patients to seek immediate medical attention if any signs or symptoms of thrombotic microangiopathy occur [see Warnings and Precautions (5.6)].

Hepatotoxicity

Advise patients to contact their healthcare providers if they experience jaundice or right upper quadrant abdominal pain [see Warnings and Precautions (5.7)].

Other Adverse Reactions

Advise patients to contact their healthcare providers if they experience signs and symptoms of acute febrile neutrophilic dermatosis (Sweet's syndrome), Stevens-Johnson syndrome, transverse myelitis, posterior reversible encephalopathy syndrome, tumor lysis syndrome, herpes zoster, cataracts, dry eyes, blurred vision, conjunctivitis and thrombotic thrombocytopenic purpura [see Adverse Reactions (6.1)].

Embryo-Fetal Toxicity

Advise pregnant women and females of reproductive potential of the potential risk to a fetus. Advise females of reproductive potential to inform their healthcare provider of a known or suspected pregnancy [see Warnings and Precautions (5.8) and Use in Specific Populations (8.1)].

Advise females of reproductive potential to use effective contraception during treatment with NINLARO and for 90 days following the last dose. Advise women using hormonal contraceptives to also use a barrier method of contraception [see Use in Specific Populations (8.1)].

Advise males with female partners of reproductive potential to use effective contraception during treatment with NINLARO and for 90 days following the last dose [see Use in Specific Populations (8.1)].

Lactation

Advise women not to breastfeed during treatment with NINLARO and for 90 days after the last dose [see Use in Specific Populations (8.2)].

Concomitant Medications

Advise patients to speak with their healthcare providers about any other medication they are currently taking and before starting any new medications.

Distributed by:
Takeda Pharmaceuticals America, Inc.
Cambridge, MA 02142

NINLARO is a registered trademark of Millennium Pharmaceuticals, Inc.

©2024 Takeda Pharmaceuticals U.S.A., Inc. All rights reserved.

For more information, you may also go to www.NINLARO.com or call 1-844-617-6468.

IXB349 R10

PATIENT INFORMATION
NINLARO® (nin-LAR-oh)
(ixazomib)
capsules

NINLARO is used with two other prescription medicines called REVLIMID® (lenalidomide) and dexamethasone. Read the Medication Guide that comes with REVLIMID® (lenalidomide). You can ask your healthcare provider or pharmacist for information about dexamethasone.

What is NINLARO?
NINLARO is a prescription medicine used to treat multiple myeloma in combination with the medicines REVLIMID® (lenalidomide) and dexamethasone, in people who have received at least one prior treatment for their multiple myeloma.
NINLARO should not be used to treat people:

- who are receiving maintenance treatment, or
- who have been newly diagnosed with multiple myeloma, unless they are participants in a controlled clinical trial.

It is not known if NINLARO is safe and effective in children.

Before taking NINLARO, tell your healthcare provider about all of your medical conditions, including if you:

- have liver problems
- have kidney problems or are on dialysis
- are pregnant or plan to become pregnant. NINLARO can harm your unborn baby.
  Females who are able to become pregnant:
  - Avoid becoming pregnant during treatment with NINLARO.
  - Your healthcare provider will do a pregnancy test before you start treatment with NINLARO.
  - You should use effective non-hormonal birth control during treatment and for 90 days after your last dose of NINLARO. If using hormonal contraceptives (for example, birth control pills), you should also use an additional barrier method of contraception (for example, diaphragm or condom). Talk to your healthcare provider about birth control methods that may be right for you during this time.
  - Tell your healthcare provider right away if you become pregnant or think you may be pregnant during treatment with NINLARO.
  Males with female partners who are able to become pregnant:
  - You should use effective birth control during treatment and for 90 days after your last dose of NINLARO.
  - Tell your healthcare provider right away if your partner becomes pregnant or thinks she may be pregnant while you are being treated with NINLARO.
- are breastfeeding or plan to breastfeed. It is not known if NINLARO passes into breast milk, if it affects an infant who is breastfed, or breast milk production. Do not breastfeed during treatment with NINLARO and for 90 days after your last dose of NINLARO.

Tell your healthcare provider about all the medicines you take, including prescription and over-the-counter medicines, vitamins, and herbal supplements. Talk to your healthcare provider before starting any new medicines during treatment with NINLARO.

How should I take NINLARO?

- Take NINLARO exactly as your healthcare provider tells you to take it. Do not change your dose or stop taking NINLARO without talking to your healthcare provider first.
- NINLARO is taken in "cycles." Each cycle lasts 4 weeks (28 days).
  - The usual dose of NINLARO is 1 capsule taken 1 time each week, on the same day of the week for the first 3 weeks of each cycle.
  - Take each dose of NINLARO at about the same time of day.
  - Take REVLIMID (lenalidomide) and dexamethasone exactly as your healthcare provider tells you to.
  - Your healthcare provider will do blood tests during treatment with NINLARO to check for side effects.
  - Your healthcare provider may change your dose or stop NINLARO, REVLIMID (lenalidomide), or dexamethasone if you have side effects.
- Take NINLARO at least 1 hour before or at least 2 hours after food.
- On the days that you take both NINLARO and dexamethasone, do not take NINLARO and dexamethasone at the same time. Take dexamethasone with food.
- Swallow NINLARO capsules whole with water. Do not crush, chew or open the capsule.
- Avoid direct contact with the capsule contents. If you accidentally get powder from the NINLARO capsule on your skin, wash the area well with soap and water. If you accidentally get powder from the NINLARO capsule in your eyes, flush your eyes well with water.
- If you miss a dose of NINLARO, or if you are late taking a dose, take the dose as long as the next scheduled dose is more than 3 days (72 hours) away. Do not take a missed dose of NINLARO if it is within 3 days (72 hours) of your next scheduled dose.
- If you vomit after taking a dose of NINLARO, do not repeat the dose. Take your next dose of NINLARO on the next scheduled day and time.
- Your healthcare provider may prescribe a medicine to take with NINLARO to decrease the risk of the chicken pox virus (herpes zoster) coming back (reactivation).
- Taking too much NINLARO (overdose) can cause serious side effects, including death. If you take more NINLARO than instructed by your healthcare provider, call your healthcare provider right away or go to the nearest hospital emergency room right away. Take your medicine pack with you.

What are the possible side effects of NINLARO?
NINLARO may cause serious side effects, including:

- Low platelet counts (thrombocytopenia). Low platelet counts are common with NINLARO, and can sometimes be serious. You may need platelet transfusions if your counts are too low. Tell your healthcare provider if you have any signs of low platelet counts, including bleeding and easy bruising.
- Stomach and intestinal (gastrointestinal) problems. Diarrhea, constipation, nausea, and vomiting are common with NINLARO, and can sometimes be severe. Call your healthcare provider if you get any of these symptoms and they do not go away during treatment with NINLARO. Your healthcare provider may prescribe medicine to help treat your symptoms.
- Nerve problems. Nerve problems are common with NINLARO and may also be severe. Tell your healthcare provider if you get any new or worsening symptoms, including:

- tingling
- numbness
- pain

- a burning feeling in your feet or hands
- weakness in your arms or legs

- Swelling. Swelling is common with NINLARO and can sometimes be severe. Tell your healthcare provider if you develop swelling in your face, arms, hands, legs, ankles, or feet, or if you gain weight from swelling.
- Skin reactions. Rashes are common with NINLARO. NINLARO can cause rashes and other skin reactions that can be serious and can lead to death. Tell your healthcare provider right away if you get a new or worsening rash, severe blistering or peeling of the skin, or mouth sores.
- Thrombotic microangiopathy (TMA). This is a condition involving blood clots and injury to small blood vessels that may cause harm to your kidneys, brain, and other organs, and may lead to death. Get medical help right away if you get any of the following signs or symptoms during treatment with NINLARO:

- fever
- bruising
- nose bleeds

- tiredness
- decreased urination

- Liver problems. Tell your healthcare provider if you get these signs of a liver problem:
  - yellowing of your skin or the whites of your eyes
  - pain in your right upper stomach-area (abdomen)

Other common side effects of NINLARO include:

- low white blood cell counts (neutropenia)

- bronchitis

Tell your healthcare provider if you get new or worsening signs or symptoms of the following during treatment with NINLARO:

- skin rash and pain (shingles) due to reactivation of the chicken pox virus (herpes zoster)
- blurred vision or other changes in your vision, dry eye and pink eye (conjunctivitis)

These are not all the possible side effects of NINLARO.
Call your healthcare provider for medical advice about side effects. You may report side effects to FDA at 1-800-FDA-1088.

How should I store NINLARO?

- Store NINLARO at room temperature. Do not store above 86°F (30°C).
- Do not freeze NINLARO.
- Store NINLARO capsules in the original packaging until just before each use.
- Ask your pharmacist or healthcare provider about how to dispose of (throw away) unused NINLARO.

Keep NINLARO and all medicines out of the reach of children.

General information about the safe and effective use of NINLARO.
Medicines are sometimes prescribed for purposes other than those listed in a Patient Information leaflet. Do not use NINLARO for a condition for which it was not prescribed. Do not give NINLARO to other people, even if they have the same symptoms that you have. It may harm them. You can ask your pharmacist or healthcare provider for information about NINLARO that is written for healthcare professionals.

What are the ingredients in NINLARO?
Active ingredient: ixazomib
Inactive ingredients: microcrystalline cellulose, magnesium stearate, and talc
Capsule shells: gelatin and titanium dioxide. The 4 mg capsule shell contains red and yellow iron oxide. The 3 mg capsule shell contains black iron oxide. The 2.3 mg capsule shell contains red iron oxide. The printing ink contains shellac, propylene glycol, potassium hydroxide, and black iron oxide.

Distributed by:
Takeda Pharmaceuticals America, Inc.
Cambridge, MA 02142
NINLARO is a registered trademark of Millennium Pharmaceuticals, Inc.
©2024 Takeda Pharmaceuticals U.S.A., Inc. All rights reserved.
For more information, you may also go to www.NINLARO.com or call 1-844-617-6468.
IXB349 R10

This Patient Information has been approved by the U.S. Food and Drug Administration.

Revised: July/2024

PRINCIPAL DISPLAY PANEL - 4 mg Capsule Blister Pack

Rx only NDC 63020-400-03

NINLARO®
(ixazomib) capsules

4 mg per capsule

Contains 3 Capsules

Please read Package Insert before use.

Lift to Open

Takeda

PRINCIPAL DISPLAY PANEL - 3 mg Capsule Blister Pack

Rx only NDC 63020-390-03

NINLARO®
(ixazomib) capsules

3 mg per capsule

Contains 3 Capsules

Please read Package Insert before use.

Lift to Open

Takeda

PRINCIPAL DISPLAY PANEL - 2.3 mg Capsule Blister Pack

Rx only NDC 63020-230-03

NINLARO®
(ixazomib) capsules

2.3 mg per capsule

Contains 3 Capsules

Please read Package Insert before use.

Lift to Open

Takeda